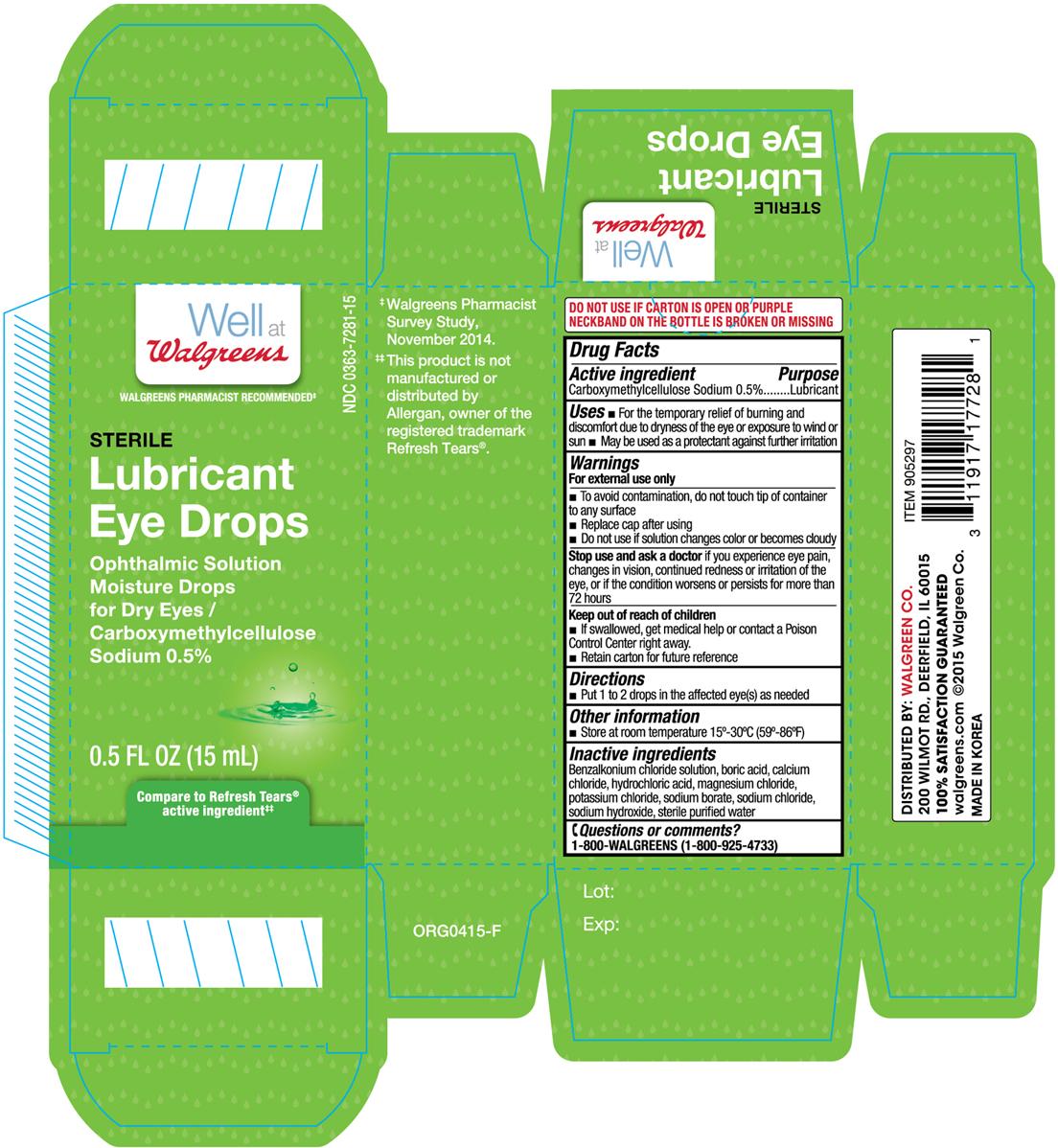 DRUG LABEL: Well at Walgreens Sterile Lubricant Eye
NDC: 0363-7281 | Form: SOLUTION/ DROPS
Manufacturer: Walgreens Company
Category: otc | Type: HUMAN OTC DRUG LABEL
Date: 20150922

ACTIVE INGREDIENTS: CARBOXYMETHYLCELLULOSE SODIUM 5 mg/1 mL
INACTIVE INGREDIENTS: BENZALKONIUM CHLORIDE; BORIC ACID; CALCIUM CHLORIDE; HYDROCHLORIC ACID; MAGNESIUM CHLORIDE; POTASSIUM CHLORIDE; SODIUM BORATE; SODIUM CHLORIDE; SODIUM HYDROXIDE; WATER

Active ingredient Purpose

Carboxymethylcellulose Sodium 0.5%.................................. Lubricant

Uses

- For the temporary relief of burning and discomfort due to dryness of the eye or exposure to wind or sun
- May be used as a protectant against further irritation

Warnings

For external use only

- To avoid contamination, do not touch tip of container to any surface
- Replace cap after using
- Do not use if solution changes color or becomes cloudy

Stop use and ask a doctor if you experience eye epain, changes in vision, continued redness or irritation of the eye, or if the condition worsens or persists for more than 72 hours

Keep out of reach of children

- If swallowed, get medical help or contact a Poison Control Center right away.
- Retain carton for future reference

Directions

- Put 1 to 2 drops in the affected eye(s) as needed

Other information

- Store at room temperature 15°-30°C (59°-86°F)

Inactive ingredients

Benzalkonium chloride solution, boric acid, calcium chloride, hydrochloric acid, magnesium chloride, potassium chloride, sodium borate, sodium chloride, sodium hydroxide, sterile purified water

DOSAGE AND ADMINISTRATION

Distributed by:

Walgreen Co.

200 Wilmot Rd.

Deerfield, IL 60015

Made in Korea